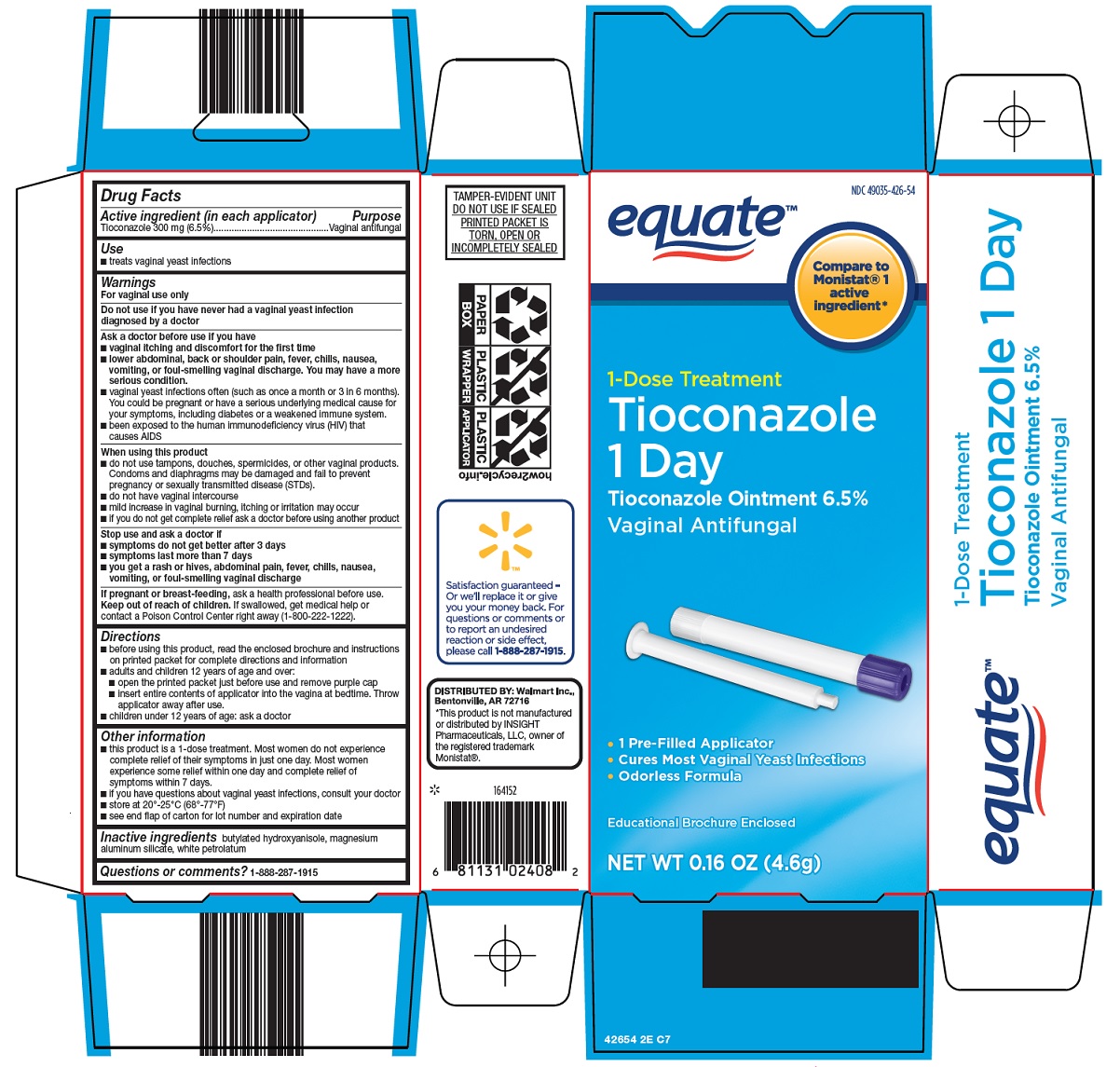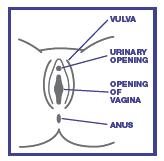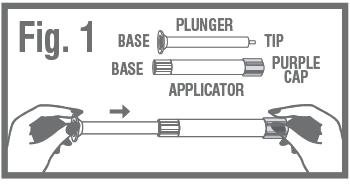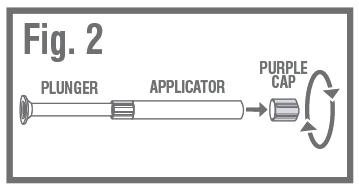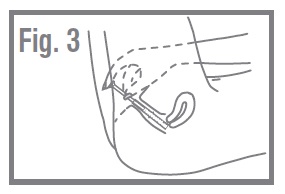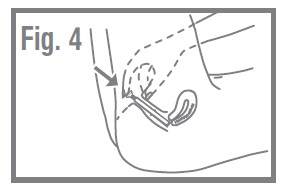 DRUG LABEL: Equate tioconazole 1 day
NDC: 49035-426 | Form: OINTMENT
Manufacturer: Wal-Mart Stores Inc
Category: otc | Type: HUMAN OTC DRUG LABEL
Date: 20250811

ACTIVE INGREDIENTS: TIOCONAZOLE 6.5 g/100 g
INACTIVE INGREDIENTS: BUTYLATED HYDROXYANISOLE; MAGNESIUM ALUMINUM SILICATE; PETROLATUM

Wal-Mart Tioconazole 1 Day Drug Facts

Active ingredient (in each applicator)

Tioconazole 300 mg (6.5%)

Purpose

Vaginal antifungal

Use

- treats vaginal yeast infections

Warnings

For vaginal use only

Do not use

if you have never had a vaginal yeast infection diagnosed by a doctor

Ask a doctor before use if you have

- vaginal itching and discomfort for the first time
- lower abdominal, back or shoulder pain, fever, chills, nausea, vomiting, or foul-smelling vaginal discharge. You may have a more serious condition.
- vaginal yeast infections often (such as once a month or 3 in 6 months). You could be pregnant or have a serious underlying medical cause for your symptoms, including diabetes or a weakened immune system.
- been exposed to human immunodeficiency virus (HIV) that causes AIDS

When using this product

- do not use tampons, douches, spermicides, or other vaginal products. Condoms and diaphragms may be damaged and fail to prevent pregnancy or sexually transmitted disease (STDs).
- do not have vaginal intercourse
- mild increase in vaginal burning, itching or irritation may occur
- if you do not get complete relief ask a doctor before using another product

Stop use and ask a doctor if

- symptoms do not get better after 3 days
- symptoms last more than 7 days
- you get a rash or hives, abdominal pain, fever, chills, nausea, vomiting, or foul-smelling vaginal discharge

If pregnant or breast-feeding,

ask a health professional before use.

Keep out of reach of children.

If swallowed, get medical help or contact a Poison Control Center right away (1-800-222-1222).

Directions

- before using this product, read the enclosed brochure and instructions on printed packet for complete directions and information
- adults and children 12 years of age and over:
- open the printed packet just before use and remove purple cap
- insert entire contents of applicator into the vagina at bedtime. Throw applicator away after use.
- children under 12 years of age: ask a doctor

Other information

- this product is a 1-dose treatment. Most women do not experience complete relief of their symptoms in just one day. Most women experience some relief within one day and complete relief of symptoms within 7 days.
- if you have questions about vaginal yeast infections, consult your doctor
- store at 20° - 25°C (68° - 77°F)
- see end flap of carton for lot number and expiration date

Inactive ingredients

butylated hydroxyanisole, magnesium aluminum silicate, white petrolatum

Questions or comments?

1-888-287-1915

Consumer Information

1-DOSE TREATMENT

Tioconazole Ointment 6.5%

VAGINAL ANTIFUNGAL

EDUCATIONAL BROCHURE

Please read this educational brochure completely before using this product.

USE: treats vaginal yeast infections

1 THIS PRODUCT CURES MOST RECURRENT VAGINAL YEAST INFECTIONS

IF THIS IS THE FIRST TIME YOU HAVE HAD VAGINAL ITCH AND DISCOMFORT, CONSULT YOUR DOCTOR. IF YOU HAVE HAD A DOCTOR DIAGNOSE A VAGINAL YEAST INFECTION BEFORE AND HAVE THE SAME SYMPTOMS NOW, USE THIS OINTMENT AS DIRECTED. THIS PRODUCT IS FOR THE TREATMENT OF RECURRENT VAGINAL YEAST INFECTIONS ONLY. IT DOES NOT TREAT OTHER INFECTIONS AND DOES NOT PREVENT PREGNANCY.

This product, a vaginal ointment that contains an antifungal medicine, works to cure most recurrent vaginal yeast infections by killing the overgrowth of yeast.

2 WHAT IS A VAGINAL YEAST INFECTION (CANDIDIASIS)?

A yeast infection is caused by an organism called Candida, which is a type of yeast. Healthy women usually have this yeast in the vagina. Either an overgrowth or rapid growth of this yeast can cause a vaginal yeast infection. The symptoms of a vaginal yeast infection can include any or all of the following:

- Vaginal itching – Itching can range from mild to intense.
- Vaginal discharge – This discharge may be thick like paste or lumpy like cottage cheese.
- Vaginal soreness, burning or irritation – The vagina can feel sore inside or there can be a burning sensation, particularly during vaginal intercourse.
- Rash or redness – Rash or redness may occur around the vagina (vulvar irritation).

NOTE: Vaginal discharge that is different from the above, for example, a yellow/green discharge or a discharge that smells "fishy" (foul-smelling), may indicate that you have something other than a yeast infection. If this is the case, you should consult your doctor before using this product.

3 WHAT ARE THE REASONS YOU GET VAGINAL YEAST INFECTIONS?

There are several conditions that can cause too much yeast to grow inside the vagina such as:

- Hormonal changes – Changes in hormonal levels can occur during pregnancy, with the use of some birth control pills, and just before a woman's menstrual period.
- Antibiotics – Because antibiotics can kill the normal bacteria in the vagina, yeast may grow very quickly.
- Diabetes – Diabetes can also make a woman more likely to get a vaginal yeast infection.
- Human Immunodeficiency Virus (HIV) – Various medical conditions can damage the body's normal defenses against infection. One of the most serious of these conditions is infection with the human immunodeficiency virus (HIV -the virus that causes AIDS). Infection with HIV causes the body to be more susceptible to infections, including vaginal yeast infections. Women with HIV infection may have frequent vaginal yeast infections or, especially, vaginal yeast infections that do not clear up easily with proper treatment. If you may have been exposed to HIV and are experiencing either frequent recurring vaginal yeast infections or, especially, vaginal yeast infections that do not clear up easily with proper treatment, you should see your doctor promptly. If you wish further information on risk factors for HIV infection or on the relationship between recurrent or persistent vaginal yeast infections and HIV infection, please contact your doctor or the CDC National AIDS HOTLINE. The CDC phone numbers are: 1-800-232-4636 (English/Spanish), or 1-888-232-6348 (hearing impaired, TTY).

4 WARNINGS

For vaginal use only

Do not use if you have never had a vaginal yeast infection diagnosed by a doctor

Ask a doctor before use if you have

- vaginal itching and discomfort for the first time
- lower abdominal, back or shoulder pain, fever, chills, nausea, vomiting, or foul-smelling vaginal discharge. You may have a more serious condition.
- vaginal yeast infections often (such as once a month or 3 in 6 months). You could be pregnant or have a serious underlying medical cause for your symptoms, including diabetes or a weakened immune system.
- been exposed to the human immunodeficiency virus (HIV) that causes AIDS

When using this product

- do not use tampons, douches, spermicides, or other vaginal products. Condoms and diaphragms may be damaged and fail to prevent pregnancy or sexually transmitted disease (STDs).
- do not have vaginal intercourse
- mild increase in vaginal burning, itching or irritation may occur
- if you do not get complete relief ask a doctor before using another product

Stop use and ask a doctor if

- symptoms do not get better after 3 days
- symptoms last more than 7 days
- you get a rash or hives, abdominal pain, fever, chills, nausea, vomiting, or foul-smelling vaginal discharge

If pregnant or breast-feeding, ask a health professional before use.

Keep out of reach of children. If swallowed, get medical help or contact a Poison Control Center right away (1-800-222-1222).

5 WHEN CAN YOU EXPECT SYMPTOM RELIEF?

While this product is a 1-dose treatment, most women do not experience complete relief of their symptoms in just 1 day. Most women experience some improvement within 1 day and complete relief of symptoms within 7 days.

If your symptoms do not improve in 3 days or if you still have symptoms after 7 days, consult your doctor. Your doctor may recommend other treatment, or you may have a condition other than a yeast infection.

If your symptoms return within 2 months or if you think you have been exposed to the human immunodeficiency virus (HIV) that causes AIDS, consult your doctor immediately. Recurring yeast infections may be a sign of pregnancy or a serious condition, such as AIDS or diabetes.

6 HOW TO USE TIOCONAZOLE OINTMENT 6.5%

This product comes in a pre-filled, single-dose applicator.

Directions for use:

- Read the full directions printed below and on the printed packet carefully before using.
- Bedtime is the best time to apply this product.
- Open the printed packet just before use.
- Remove the applicator and plunger from the printed packet. The applicator is pre-filled with vaginal ointment.
- While firmly holding the purple-capped end of the applicator, push the tip of the plunger into the base of applicator. Fig. 1

- REMOVE PURPLE CAPfrom the top of the applicator using a pull-twist action. Fig. 2

- Lie on your back with your knees bent. Gently insert applicator into the vagina as far as it will go comfortably. Fig. 3

- Push the plunger into the applicator until it will go no farther. Withdraw the applicator and plunger and dispose of it in the wastebasket. Do not flush. Fig. 4

- DO NOT USE TAMPONS while using this medicine. Use sanitary napkins instead.

7 ADVERSE REACTIONS (SIDE EFFECTS)

A temporary increase in vaginal burning, itching and/or irritation may be experienced upon insertion of this ointment. These reactions, in addition to vaginal swelling or redness; difficulty or burning on urination; headache; abdominal pain/cramping and upper respiratory infection have been reported with the use of this product. If you experience any of these, consult your doctor.

8 COMMON QUESTIONS ABOUT VAGINAL YEAST INFECTIONS AND TIOCONAZOLE OINTMENT 6.5%

Q. Should I use this product while I have my period?

You should use this product while menstruating but you should not use tampons following application. Use sanitary napkins instead.

Q. Can I have sex while using this product?

It is generally recommended not to have vaginal intercourse the first few nights after treatment with this product.

Q. Can I use a condom or diaphragm while using this product?

No. This product contains petrolatum which may damage the latex from which condoms and diaphragms are made and may cause them to fail. This may reduce their effectiveness in preventing sexually transmitted diseases and pregnancy. You should wait 3 days after treatment to resume using condoms or your diaphragm.

Q. Does my partner need to be treated?

Yeast infections occur less frequently in men than in women. However, if your partner has any of the following symptoms: itching, redness or discomfort in the genital area, he should see a doctor and mention that you are treating a vaginal yeast infection.

Q. Can I use feminine hygiene products (such as douche) while I have a vaginal yeast infection?

It is best not to use any vaginal preparations while you have a yeast infection including douches, feminine hygiene sprays, contraceptive foams, inserts, or jellies.

9 FOR BEST RESULTS

- Wear cotton underwear and loose-fitting clothes – Yeast grow in warm, moist environments. Wearing loose-fitting, cotton clothes helps create a cooler environment, which makes it more difficult for yeast to grow.
- Change out of a wet bathing suit quickly – Dampness is more likely to encourage the growth of yeast.
- Use proper hygiene – Wipe from front to rear (away from vagina) after a bowel movement or urination.
- Discuss with your doctor any medication you are now taking – Certain types of medication can make your vagina more prone to infection.

If you have any other questions or concerns about vaginal yeast infections or of a medical nature, don't hesitate to consult your doctor.

If you have questions or comments about this product, call our toll-free number 1-800-719-9260.

CONTENTS

Active ingredient: Tioconazole 300 mg (6.5% per applicator).

Inactive ingredients: Butylated hydroxyanisole, magnesium aluminum silicate and white petrolatum.

Store at 20°-25°C (68°-77°F).

Do not use if printed packet is torn, open, or incompletely sealed.

For expiration date and lot number, see carton end flap and applicator printed packet.

Distributed By

Perrigo®

Allegan, MI 49010

: 42600 00 J4

Principal Display Panel

equate™

Compare to Monistat® 1 active ingredient

1-Dose Treatment

Tioconazole 1 Day

Tioconazole Ointment 6.5%

Vaginal Antifungal

• 1 Pre-Filled Applicator

• Cures Most Vaginal Yeast Infections

• Odorless Formula

Educational Brochure Enclosed

NET WT 0.16 OZ (4.6g)